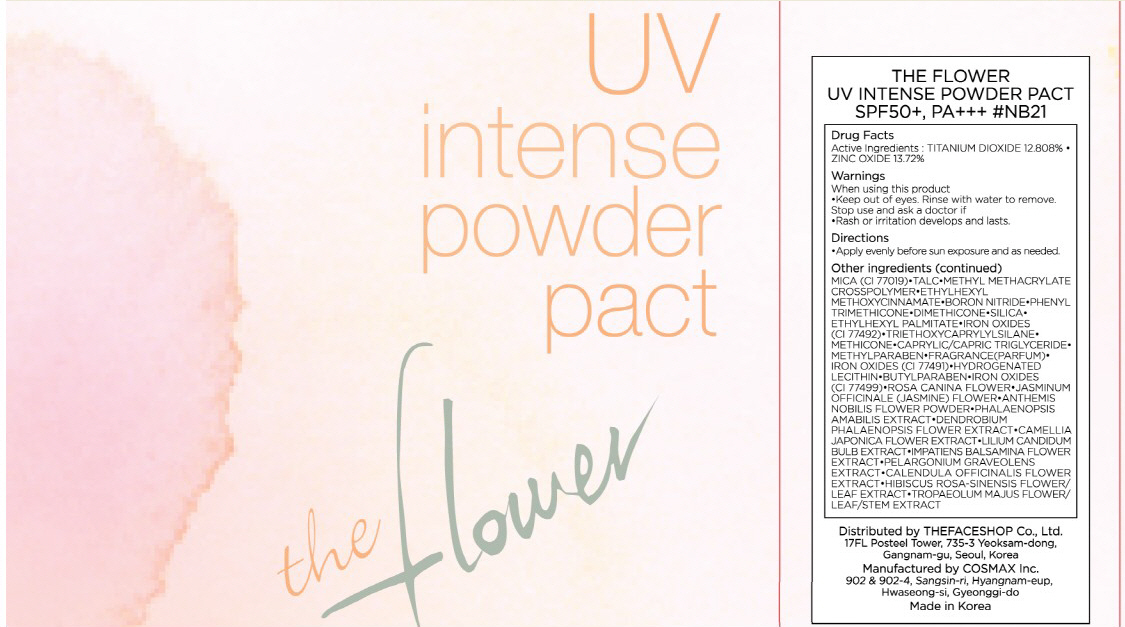 DRUG LABEL: THE FLOWER UV INTENSE PACT
NDC: 51523-023 | Form: POWDER
Manufacturer: THEFACESHOP CO., LTD.
Category: otc | Type: HUMAN OTC DRUG LABEL
Date: 20100714

ACTIVE INGREDIENTS: ZINC OXIDE 1.64 g/12 g; TITANIUM DIOXIDE 1.53 g/12 g

Drug Facts

Active Ingredients: TITANIUM DIOXIDE, ZINC OXIDE

Inactive Ingredients:
MICA(CI 77019), TALC, METHYL METHACRYLATE CROSSPOLYMER, ETHYLHEXYL METHOXYCINNAMATE, BORON NITRIDE, PHENYL TRIMETHICONE, DIMETHICONE, SILICA,
ETHYLHEXYL PALMITATE, IRON OXIDES(CI 77492), TRIETHOXYCAPRYLYLSILANE, METHICONE, CAPRYLIC / CAPRIC TRIGLYCERIDE, METHYLPARABEN, FRAGRANCE, IRON OXIDES(CI 77491), HYDROGENATED LECITHIN, BUTYLPARABEN, IRON OXIDES(CI 77499), ROSA CANINA FLOWER, JASMINUM OFFICINALE (JASMINE) FLOWER, ANTHEMIS NOBILIS FLOWER POWDER, PHALAENOPSIS AMABILIS EXTRACT, DENDROBIUM PHALAENOPSIS FLOWER EXTRACT, CAMELLIA JAPONICA FLOWER EXTRACT, LILIUM CANDIDUM BULB EXTRACT, IMPATIENS BALSAMINA FLOWER EXTRACT, PELARGONIUM GRAVEOLENS EXTRACT, CALENDULA OFFICINALIS FLOWER EXTRACT, HIBISCUS ROSA-SINENSIS FLOWER/LEAF EXTRACT, TROPAEOLUM MAJUS FLOWER/LEAF/STEM EXTRACT

Warnings:
When using this product
Keep out of eyes. Rinse with water to remove.
Stop use and ask a doctor if
Rash or irritation develops and lasts.
Directions:
Apply evenly before sun exposure and as needed.